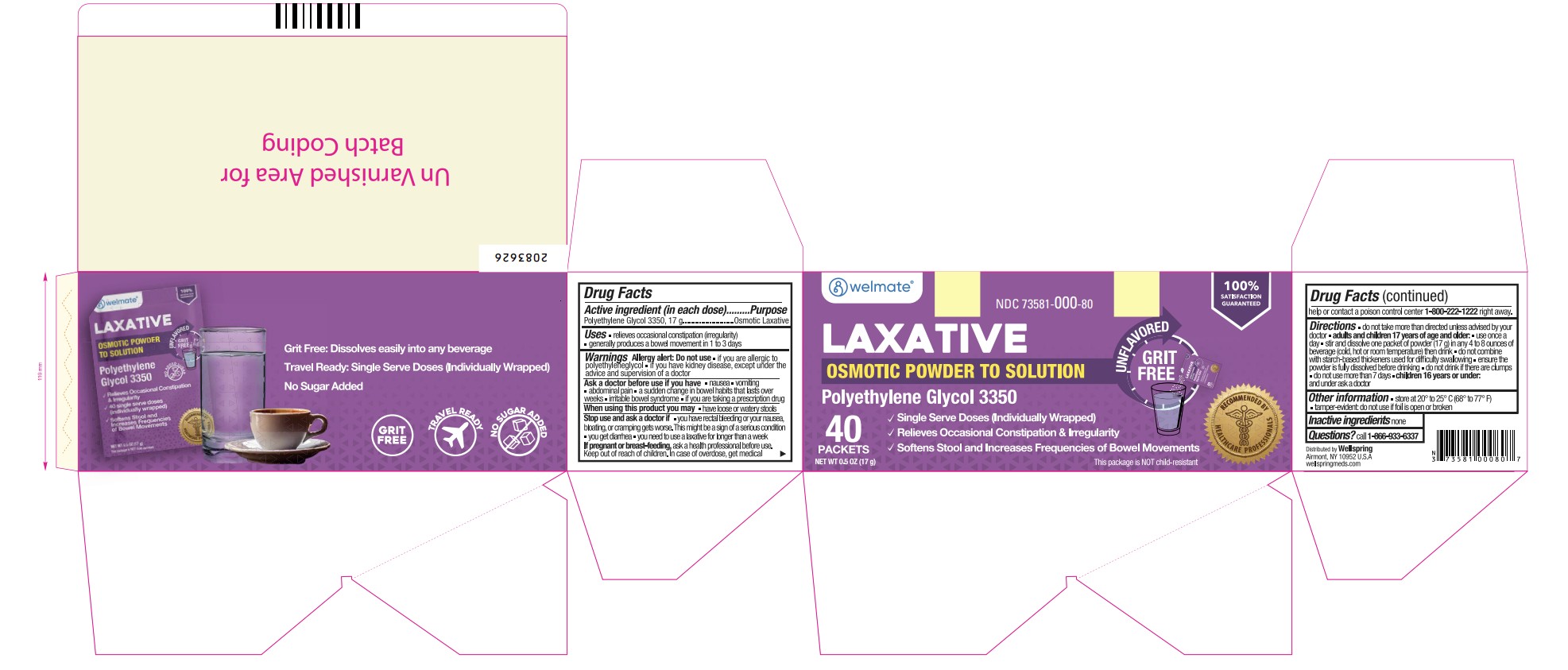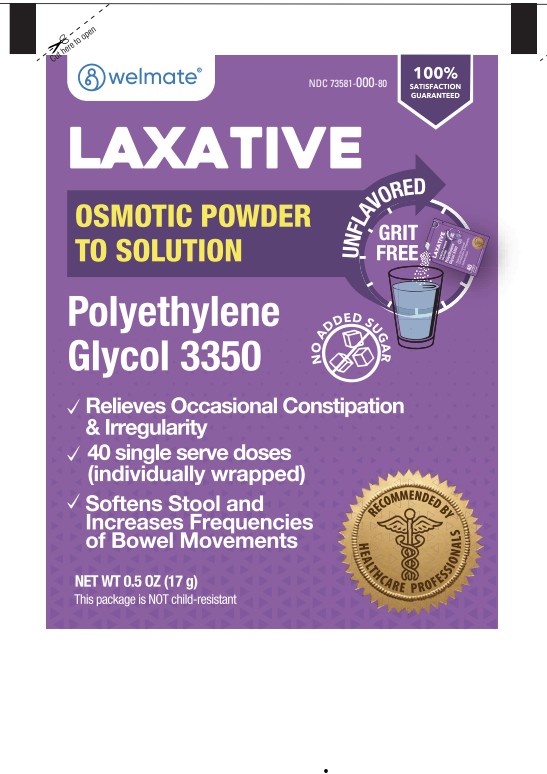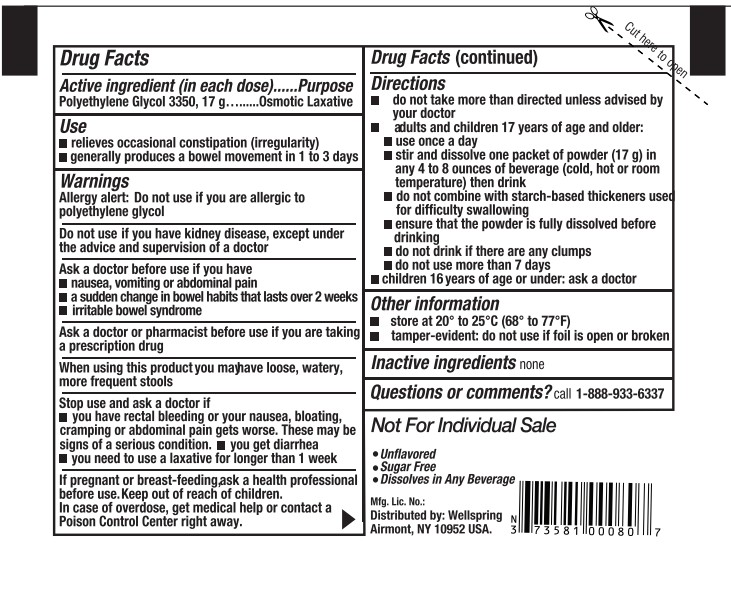 DRUG LABEL: Polyethylene Glycol 3350
NDC: 73581-913 | Form: POWDER, FOR SOLUTION
Manufacturer: YYBA Corp
Category: otc | Type: HUMAN OTC DRUG LABEL
Date: 20260113

ACTIVE INGREDIENTS: POLYETHYLENE GLYCOL 3350 17 g/1 1

Camber PEG 3350

ACTIVE INGREDIENT (IN EACH DOSE)

(Packet Only)

Polyethylene Glycol 3350, 17 g

PURPOSE

Osmotic Laxative

USE

• relieves occasional constipation (irregularity)
• generally produces a bowel movement in 1 to 3 days

WARNINGS

Allergy alert: Do not use if you are allergic to polyethylene glycol

DO NOT USE

if you have kidney disease, except under the advice and supervision of a doctor

ASK A DOCTOR BEFORE USE IF YOU HAVE

- nausea, vomiting or abdominal pain
- a sudden change in bowel habits that lasts over 2 weeks
- irritable bowel syndrome

ASK A DOCTOR OR PHARMACIST BEFORE USE IF YOU ARE

taking a prescription drug

WHEN USING THIS PRODUCT

you may have loose, watery, more frequent stools

STOP USE AND ASK A DOCTOR IF

- you have rectal bleeding or your nausea, bloating, cramping or abdominal pain gets worse. These may be signs of a serious condition.
- you get diarrhea
- you need to use a laxative for longer than 1 week

IF PREGNANT OR BREAST-FEEDING

ask a health professional before use.

KEEP OUT OF REACH OF CHILDREN

In case of overdose, get medical help or contact a Poison Control Center right away.

DIRECTIONS

(Bottle Only)

• do not take more than directed unless advised by your doctor
• the bottle top is a measuring cap marked to contain 17 grams of powder when filled to the indicated line (white section in cap)
• adults and children 17 years of age and older:

• use once a day
• fill to top of white section in cap which is marked to indicate the correct dose (17 g)

• stir and dissolve in any 4 to 8 ounces of beverage (cold, hot or room temperature) then drink

• do not combine with starch-based thickeners used for difficult swallowing
• ensure that the powder is fully dissolved before drink:iog
• do not drink if there are any clumps
• do not use more than 7 days
• children 16 years of age or under: ask a doctor

(Packet Only)

• do not take more than directed unless advised by your doctor
• adults and children 17 years of age and older:

• use once a day
• stir and dissolve one packet of powder (17 g) in any 4 to 8 ounces of beverage (cold, hot or room temperature) then drink

• do not combine with starch-based thickeners used for difficult swallowing
• ensure that the powder is fully dissolved before drink:iog
• do not drink if there are any clumps
• do not use more than 7 days
• children 16 years of age or under: ask a doctor

OTHER INFORMATION

- store at 20° to 25°C (68° to 77°F)
- tamper-evident: do not use if foil seal under cap, printed with "SEALED for YOUR PROTECTION" is missing, open or broken

INACTIVE INGREDIENTS

none

QUESTIONS OR COMMENTS

call

1-866-933-6337

PRINCIPAL DISPLAY PANEL

Polyethylene glycol 3350 powder for oral solution carton label

Polyethylene glycol 3350 powder for oral solution carton label